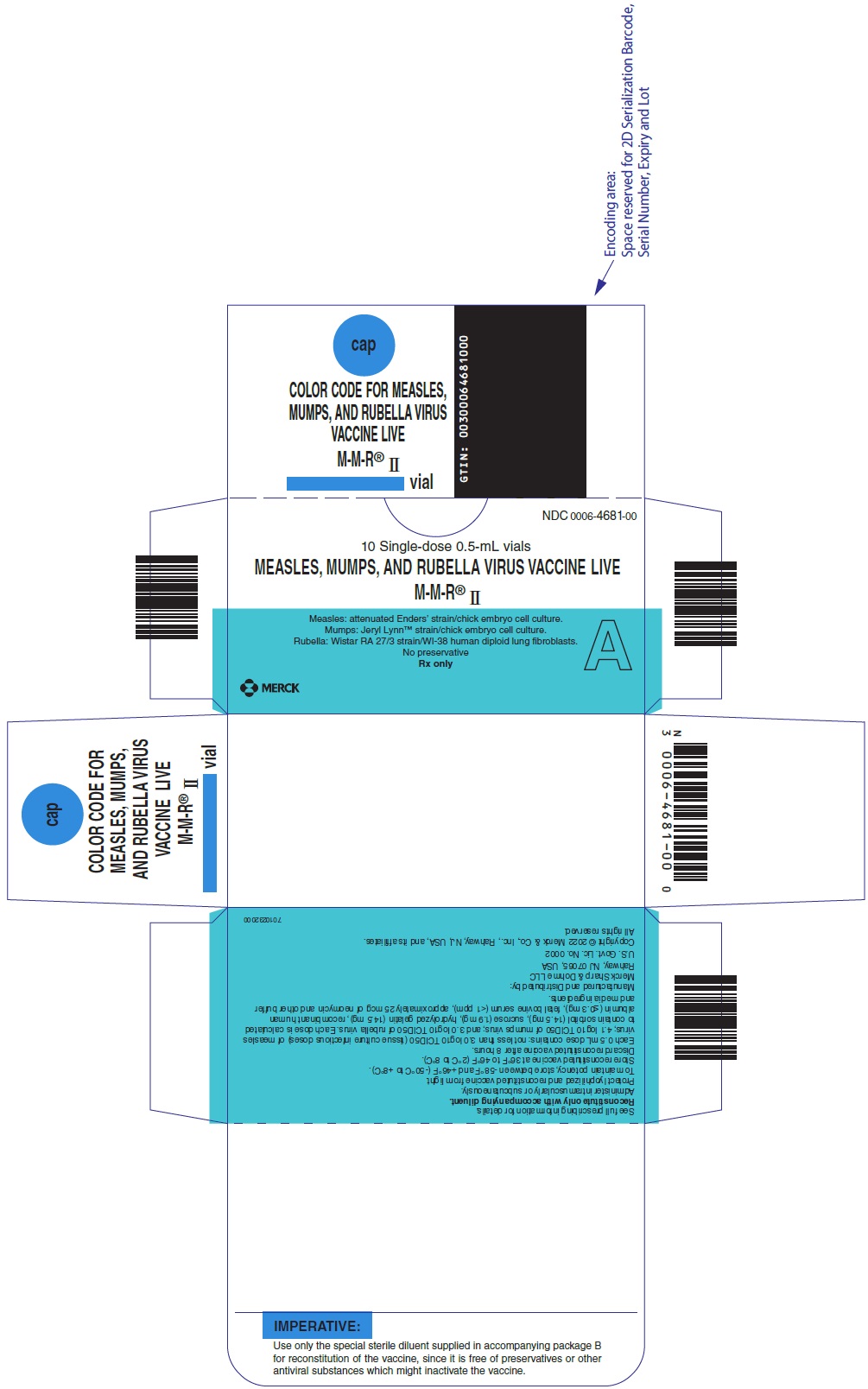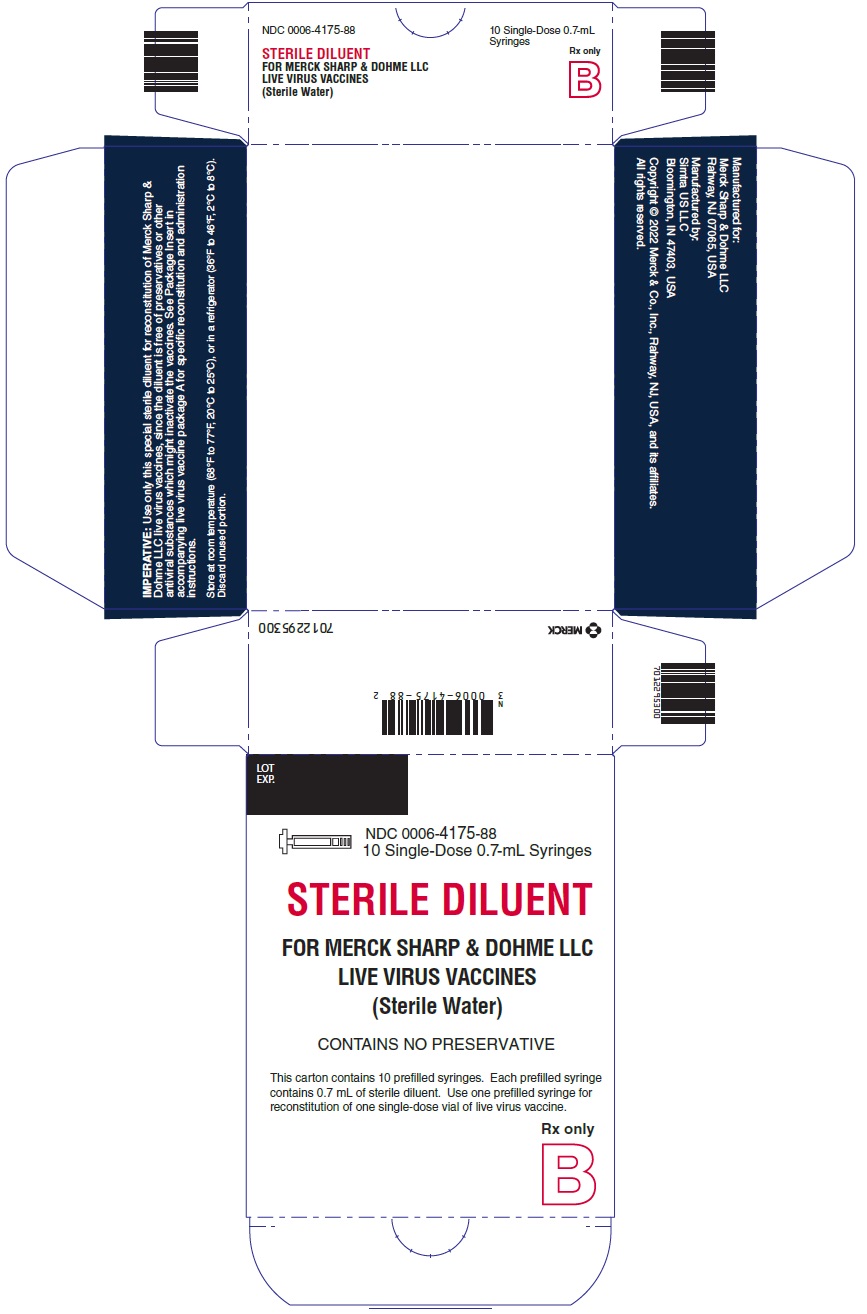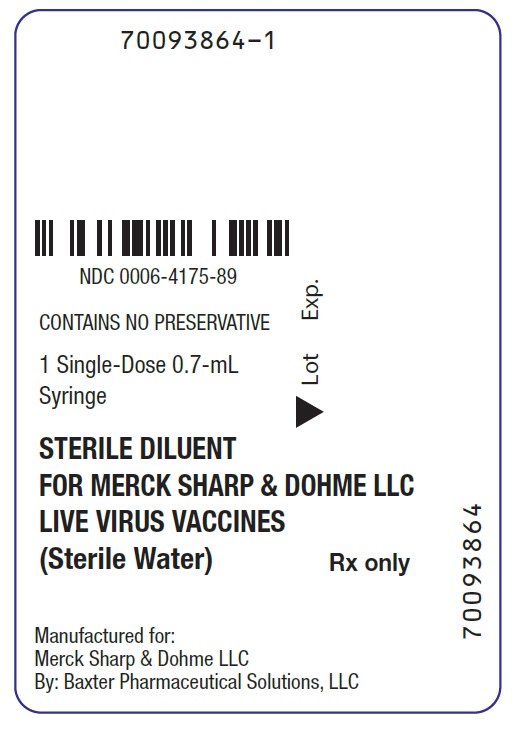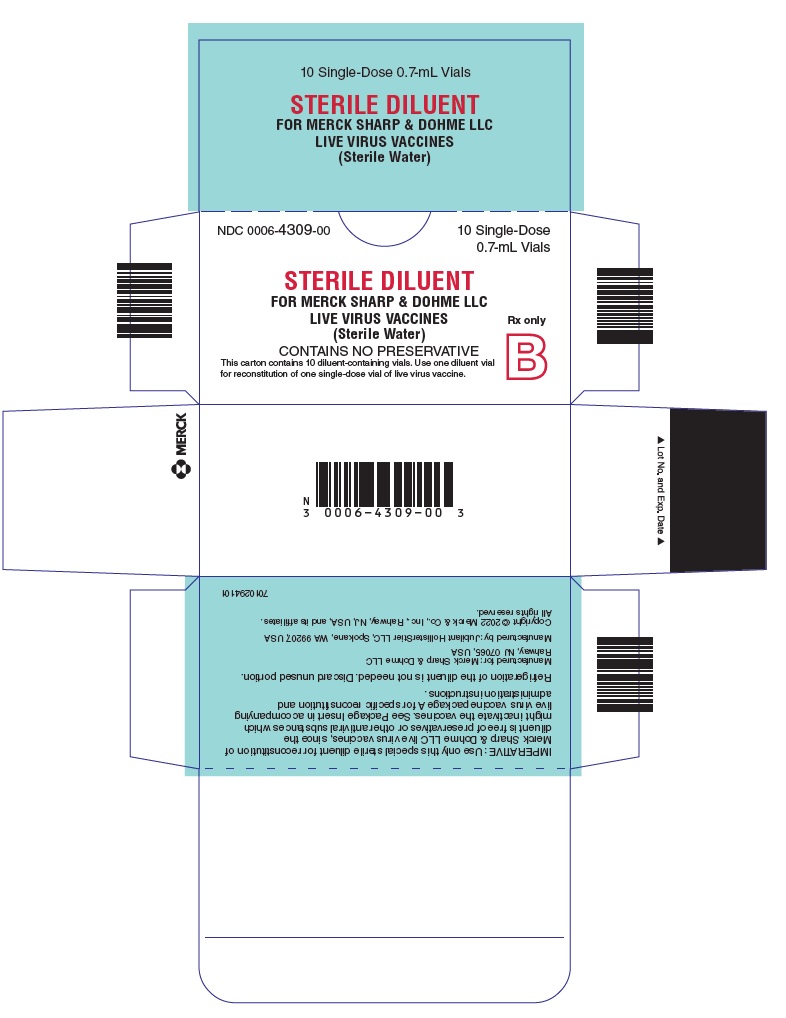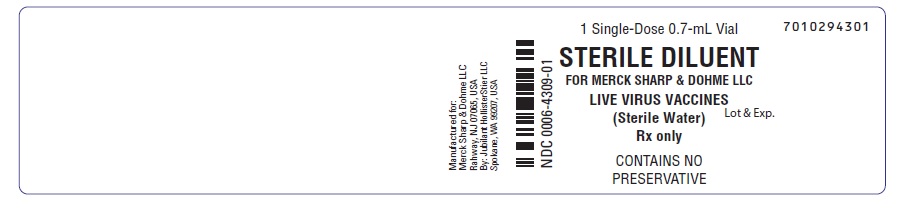 DRUG LABEL: M-M-R II
NDC: 0006-4681 | Form: INJECTION, POWDER, LYOPHILIZED, FOR SUSPENSION
Manufacturer: Merck Sharp & Dohme LLC
Category: other | Type: VACCINE LABEL
Date: 20251107

ACTIVE INGREDIENTS: MEASLES VIRUS STRAIN ENDERS' ATTENUATED EDMONSTON LIVE ANTIGEN 1000 [TCID_50]/0.5 mL; MUMPS VIRUS STRAIN B LEVEL JERYL LYNN LIVE ANTIGEN 12500 [TCID_50]/0.5 mL; RUBELLA VIRUS STRAIN WISTAR RA 27/3 LIVE ANTIGEN 1000 [TCID_50]/0.5 mL
INACTIVE INGREDIENTS: ALBUMIN BOVINE; ALBUMIN HUMAN 0.3 mg/0.5 mL; GELATIN, UNSPECIFIED 14.5 mg/0.5 mL; NEOMYCIN 25 ug/0.5 mL; SODIUM CHLORIDE; SODIUM PHOSPHATE; SORBITOL 14.5 mg/0.5 mL; SUCROSE 1.9 mg/0.5 mL

HIGHLIGHTS OF PRESCRIBING INFORMATION

These highlights do not include all the information needed to use M-M-R II safely and effectively. See full prescribing information for M-M-R II.
M-M-R® II (Measles, Mumps, and Rubella Virus Vaccine Live) for injectable suspension, for intramuscular or subcutaneous use
Initial U.S. Approval: 1978

1 INDICATIONS AND USAGE

M-M-R II is a vaccine indicated for active immunization for the prevention of measles, mumps, and rubella in individuals 12 months of age and older. (1)

2 DOSAGE AND ADMINISTRATION

For intramuscular or subcutaneous use. (2.1, 2.2)
A single dose is approximately 0.5 mL.

- The first dose is administered at 12 to 15 months of age. (2.1)
- The second dose is administered at 4 to 6 years of age. (2.1)

3 DOSAGE FORMS AND STRENGTHS

For injectable suspension. M-M-R II (approximately 0.5 mL dose) is supplied as a lyophilized vaccine to be reconstituted using accompanying sterile diluent. (3)

4 CONTRAINDICATIONS

- Hypersensitivity to any component of the vaccine. (4.1)
- Immunosuppression. (4.2)
- Moderate or severe febrile illness. (4.3)
- Active untreated tuberculosis. (4.4)
- Pregnancy. (4.5, 8.1)

5 WARNINGS AND PRECAUTIONS

- Use caution when administering M-M-R II to individuals with a history of febrile seizures. (5.1)
- Use caution when administering M-M-R II to individuals with anaphylaxis or immediate hypersensitivity following egg ingestion. (5.2)
- Use caution when administering M-M-R II to individuals with a history of thrombocytopenia. (5.3)
- Evaluate individuals for immune competence prior to administration of M-M-R II if there is a family history of congenital or hereditary immunodeficiency. (5.4)
- Immune Globulins (IG) and other blood products should not be given concurrently with M-M-R II. (5.5, 7.2)

6 ADVERSE REACTIONS

See full prescribing information for adverse reactions occurring during clinical trials or the postmarketing period. (6)

To report SUSPECTED ADVERSE REACTIONS, contact Merck Sharp & Dohme LLC at 1-877-888-4231 or VAERS at 1-800-822-7967 or www.vaers.hhs.gov .

7 DRUG INTERACTIONS

- Administration of immune globulins and other blood products concurrently with M-M-R II vaccine may interfere with the expected immune response. (7.2)
- M-M-R II vaccination may result in a temporary depression of purified protein derivative (PPD) tuberculin skin sensitivity. (7.3)

8 USE IN SPECIFIC POPULATIONS

- Pregnancy: Do not administer M-M-R II to females who are pregnant. Pregnancy should be avoided for 1 month following vaccination with M-M-R II. (4.5, 8.1, 17)

FULL PRESCRIBING INFORMATION

1 INDICATIONS AND USAGE

M-M-R II is a vaccine indicated for active immunization for the prevention of measles, mumps, and rubella in individuals 12 months of age and older.

2 DOSAGE AND ADMINISTRATION

For Intramuscular or Subcutaneous administration only.

2.1 Dose and Schedule

A single dose of M-M-R II is approximately 0.5 mL.

The first dose is administered at 12 to 15 months of age. A second dose is administered at 4 to 6 years of age.

The second dose may be administered prior to 4 years of age, provided that there is a minimum interval of one month between the doses of measles, mumps and rubella virus vaccine, live {1-2}.

Children who received an initial dose of measles, mumps and rubella vaccine prior to their first birthday should receive additional doses of vaccine at 12-15 months of age and at 4-6 years of age to complete the vaccination series [see Clinical Studies (14.2)].

For post-exposure prophylaxis for measles, administer a dose of M-M-R II vaccine within 72 hours after exposure.

2.2 Administration

The sterile diluent for M-M-R II is provided in either a vial or prefilled syringe.

Sterile Diluent Vial

Use a sterile syringe free of preservatives, antiseptics, and detergents for each injection and/or reconstitution of the vaccine because these substances may inactivate the vaccine viruses. To reconstitute, use the sterile diluent vial supplied with M-M-R II. The sterile diluent does not contain preservatives or other antiviral substances which might inactivate the vaccine viruses.

To reconstitute the vaccine, withdraw the entire volume of the supplied sterile diluent from the vial and slowly inject into the lyophilized vaccine vial. Gently agitate to dissolve completely. Discard if the lyophilized vaccine cannot be dissolved.

Parenteral drug products should be inspected visually for particulate matter and discoloration prior to administration, whenever solution and container permit. Visually inspect the vaccine before and after reconstitution prior to administration. Before reconstitution, the lyophilized vaccine is a light yellow compact crystalline plug. M-M-R II, when reconstituted, is a clear yellow liquid. Do not use the reconstituted vaccine if particulates are present or if it appears discolored.

Withdraw and administer the entire volume of the reconstituted vaccine.

Administer M-M-R II immediately after reconstitution. If not used immediately, the reconstituted vaccine may be stored between 36°F to 46°F (2°C to 8°C), protected from light, for up to 8 hours. Discard reconstituted vaccine if it is not used within 8 hours.

Sterile Diluent Prefilled Syringe

To reconstitute, use the sterile diluent prefilled syringe supplied with the vaccine since it does not contain preservatives or other antiviral substances which might inactivate the vaccine viruses.

Attach a needle to the prefilled syringe.

Reconstitute the vaccine by slowly injecting the entire volume of sterile diluent contained in the prefilled syringe into the lyophilized vaccine vial. Gently agitate to dissolve completely. Discard if the lyophilized vaccine cannot be dissolved.

Parenteral drug products should be inspected visually for particulate matter and discoloration prior to administration, whenever solution and container permit. Visually inspect the vaccine before and after reconstitution prior to administration. Before reconstitution, the lyophilized vaccine is a light yellow compact crystalline plug. M-M-R II, when reconstituted, is a clear yellow liquid. Do not use the reconstituted vaccine if particulates are present or if it appears discolored.

Withdraw and administer the entire volume of the reconstituted vaccine.

Administer M-M-R II immediately after reconstitution. If not used immediately, the reconstituted vaccine may be stored between 36°F to 46°F (2°C to 8°C), protected from light, for up to 8 hours. Discard reconstituted vaccine if it is not used within 8 hours.

3 DOSAGE FORMS AND STRENGTHS

For injectable suspension. M-M-R II vaccine is supplied as a single dose vial of lyophilized vaccine to be reconstituted using the accompanying sterile diluent [see Dosage and Administration (2.2) and How Supplied/Storage and Handling (16)]. A single dose after reconstitution is approximately 0.5 mL.

4 CONTRAINDICATIONS

4.1 Hypersensitivity

Do not administer M-M-R II vaccine to individuals with a history of hypersensitivity to any component of the vaccine (including gelatin) {3} or who have experienced a hypersensitivity reaction following administration of a previous dose of M-M-R II vaccine or any other measles, mumps and rubella-containing vaccine. Do not administer M-M-R II vaccine to individuals with a history of anaphylaxis to neomycin [see Description (11)].

4.2 Immunosuppression

Do not administer M-M-R II vaccine to individuals who are immunodeficient or immunosuppressed due to disease or medical therapy. Measles inclusion body encephalitis {4} (MIBE), pneumonitis {5} and death as a direct consequence of disseminated measles vaccine virus infection have been reported in immunocompromised individuals inadvertently vaccinated with measles-containing vaccine. In this population, disseminated mumps and rubella vaccine virus infection have also been reported.

4.3 Moderate or Severe Febrile Illness

Do not administer M-M-R II vaccine to individuals with an active febrile illness with fever >101.3°F (>38.5°C).

4.4 Active Untreated Tuberculosis

Do not administer M-M-R II vaccine to individuals with active untreated tuberculosis (TB).

4.5 Pregnancy

Do not administer M-M-R II to individuals who are pregnant or who are planning on becoming pregnant within the next month [see Use in Specific Populations (8.1) and Patient Counseling Information (17)].

5 WARNINGS AND PRECAUTIONS

5.1 Febrile Seizure

There is a risk of fever and associated febrile seizure in the first 2 weeks following immunization with M-M-R II vaccine. For children who have experienced a previous febrile seizure (from any cause) and those with a family history of febrile seizures there is a small increase in risk of febrile seizure following receipt of M-M-R II vaccine [see Adverse Reactions (6)].

5.2 Hypersensitivity to Eggs

Individuals with a history of anaphylactic, anaphylactoid, or other immediate reactions (e.g., hives, swelling of the mouth and throat, difficulty breathing, hypotension, or shock) subsequent to egg ingestion may be at an enhanced risk of immediate-type hypersensitivity reactions after receiving M-M-R II vaccine. The potential risks and known benefits should be evaluated before considering vaccination in these individuals.

5.3 Thrombocytopenia

Transient thrombocytopenia has been reported within 4-6 weeks following vaccination with measles, mumps and rubella vaccine. Carefully evaluate the potential risk and benefit of vaccination in children with thrombocytopenia or in those who experienced thrombocytopenia after vaccination with a previous dose of measles, mumps, and rubella vaccine {6-8} [see Adverse Reactions (6)].

5.4 Family History of Immunodeficiency

Vaccination should be deferred in individuals with a family history of congenital or hereditary immunodeficiency until the individual’s immune status has been evaluated and the individual has been found to be immunocompetent.

5.5 Immune Globulins and Other Blood Products

Immune Globulins (IG) and other blood products should not be given concurrently with M-M-R II [see Drug Interactions (7.2)]. These products may contain antibodies that interfere with vaccine virus replication and decrease the expected immune response.

The U.S. Centers for Disease Control and Prevention (CDC) has specific recommendations for intervals between administration of antibody containing products and live virus vaccines.

6 ADVERSE REACTIONS

The following adverse reactions include those identified during clinical trials or reported during post-approval use of M-M-R II vaccine or its individual components.

Body as a Whole

Panniculitis; atypical measles; fever; headache; dizziness; malaise; irritability.

Cardiovascular System

Vasculitis.

Digestive System

Pancreatitis; diarrhea; vomiting; parotitis; nausea.

Hematologic and Lymphatic Systems

Thrombocytopenia; purpura; regional lymphadenopathy; leukocytosis.

Immune System

Anaphylaxis, anaphylactoid reactions, angioedema (including peripheral or facial edema) and bronchial spasm.

Musculoskeletal System

Arthritis; arthralgia; myalgia.

Nervous System

Encephalitis; encephalopathy; measles inclusion body encephalitis (MIBE) subacute sclerosing panencephalitis (SSPE); Guillain-Barré Syndrome (GBS); acute disseminated encephalomyelitis (ADEM); transverse myelitis; febrile convulsions; afebrile convulsions or seizures; ataxia; polyneuritis; polyneuropathy; ocular palsies; paresthesia; syncope.

Respiratory System

Pneumonia; pneumonitis; sore throat; cough; rhinitis.

Skin

Stevens-Johnson syndrome; acute hemorrhagic edema of infancy; Henoch-Schönlein purpura; erythema multiforme; urticaria; rash; measles like rash; pruritus; injection site reactions (pain, erythema, swelling and vesiculation); chronic cutaneous granulomas with rubella vaccine virus detected by biopsy.

Special Senses — Ear

Nerve deafness; otitis media.

Special Senses — Eye

Retinitis; optic neuritis; papillitis; conjunctivitis.

Urogenital System

Epididymitis; orchitis.

In a randomized open-label clinical trial (NCT00432523), conducted in France and Germany, 752 children 12 months through 18 months of age received M-M-R II concomitantly administered with VARIVAX at a separate site, by either the intramuscular (n=374) or subcutaneous (n=378) route. In the overall population, 55.3% were male and the median age was 13.2 months. Local and systemic solicited adverse reactions were recorded by parents or guardians using standardized diary cards. Local solicited reactions were recorded for 4 days after vaccination, and systemic solicited adverse reactions were recorded for 42 days after vaccination. In the event that a participant experienced a rash or a mumps-like illness, parents and/or guardians were instructed to contact the investigator for an examination as soon as possible and no later than 72 hours following onset of symptoms. The nature of any rash was characterized by principal investigator either as measles-like, rubella-like, varicella-like or “other”. Study investigators reviewed the diary card with the participant or participant’s legal guardian 42 days after vaccination to ensure consistency with protocol definitions. Table 1 below presents the frequency of solicited adverse reactions based on the final assessment by the study investigators.

Table 1: Proportion of Participants Reporting Solicited Adverse Reactions Following Vaccination with M-M-R II, Concomitantly Administered with VARIVAX, by the Intramuscular or Subcutaneous Route
 | INTRAMUSCULAR N=374 % | SUBCUTANEOUS N=376 %
Solicited injection-site reactions at MMR injection-site (Days 0 to 4) [During the post vaccination monitoring period (0-42 days), 3 participants experienced a varicella-like injection-site rash at the M-M-R II injection site. All were reported in the subcutaneous group.]
Erythema [Intensity of injection site reaction: mild or ≤2.5 cm; moderate or >2.5 to ≤5.0 cm; severe or >5.0 cm.] | 10.4 | 16.2
Mild | 8.8 | 13.0
Moderate | 0.8 | 3.2
Severe | 0 | 0
Missing | 0.8 | 0
Pain [Intensity of pain: mild: awareness of symptom but easily tolerated; moderate: definitely acting like something is wrong; severe: extremely distressed or unable to do usual activities.] | 7.0 | 7.2
Mild | 5.1 | 5.9
Moderate | 1.9 | 1.3
Severe | 0 | 0
Swelling | 1.9 | 5.3
Mild | 1.1 | 2.9
Moderate | 0.5 | 1.1
Severe | 0 | 0
Missing | 0.3 | 1.3
Solicited systemic reactions (Days 0 to 42)
Measles-like rash [Testing to distinguish between rash caused by wild-type or vaccine virus was not performed. Reports of measles-, rubella-, and varicella-like rash included 3 reports of measles, 1 report of rubella, and 1 report of varicella, all with onset within 15 days post-vaccination.] | 2.9 | 2.7
Rubella-like rash | 2.7 | 2.7
Varicella-like rash | 0.5 | 3.2
Mumps-like illness | 0 | 0.3
Fever (temperature ≥38.0°C) [The percentage of fever is defined within the population who had valid temperature measurements. One participant in IM group and two participants in SC group did not have temperature measurements and were excluded from the denominator; resulting in N=373 and N=374, respectively.] , [In the IM Group 92.3% of fevers were documented using the rectal route of measurement and 7.7% of fevers were documented only by the axillary route of measurement. In the SC Group 89.6% of fevers were documented using the rectal route of measurement and 10.4% of fevers were documented only by the axillary route of measurement.] | 66.5 | 66.8
38.0-38.5°C | 20.4 | 22.2
>38.5-39.0°C | 17.4 | 16.6
>39.0-39.5°C | 14.2 | 13.4
>39.5-40.0°C | 11.8 | 11.0
>40.0°C | 2.7 | 3.7
N=total number of participants in the group

Unsolicited adverse events that occurred within 42 days following vaccination were recorded using diary cards supplemented by medical review. Data on unsolicited adverse events were transcribed into the study database during an on-site visit at day 42. The rates and types of reported adverse events (AEs) across groups were similar and included common clinical events that are often reported in the evaluated populations. Serious adverse events occurred at rates of 0.3% and 1% in the intramuscular and subcutaneous groups, respectively. One moderate intensity case of otitis media occurred in a participant in the subcutaneous group was considered related to the study vaccination.

7 DRUG INTERACTIONS

7.1 Immunosuppressive Drugs

Do not administer M-M-R II vaccine to individuals who are immunosuppressed due to medical therapy.
Vaccination with M-M-R II vaccine can result in disseminated disease due to vaccine viruses in individuals on immunosuppressive drugs [see Contraindications (4.2)].

7.2 Immune Globulins and Other Blood Products

Administration of immune globulins and other blood products concurrently with M-M-R II vaccine may interfere with the expected immune response {9-11} [see Warnings and Precautions (5.5)]. The U.S. Centers for Disease Control and Prevention (CDC) has specific recommendations for intervals between administration of antibody containing products and live virus vaccines.

7.3 Tuberculin Skin Testing

It has been reported that live attenuated measles, mumps and rubella virus vaccines given individually may result in a temporary depression of tuberculin skin sensitivity. Therefore, if a tuberculin skin test with tuberculin purified protein derivative (PPD) is to be done, it should be administered before, simultaneously with, or at least 4 to 6 weeks after vaccination with M-M-R II vaccine.

7.4 Use with Other Live Viral Vaccines

M-M-R II vaccine can be administered concurrently with other live viral vaccines. If not given concurrently, M-M-R II vaccine should be given one month before or one month after administration of other live viral vaccines to avoid potential for immune interference.

8 USE IN SPECIFIC POPULATIONS

8.1 Pregnancy

Risk Summary

M-M-R II vaccine contains live attenuated measles, mumps and rubella viruses. M-M-R II vaccine is contraindicated for use in pregnant women because infection during pregnancy with the wild-type viruses has been associated with maternal and fetal adverse outcomes.

Increased rates of spontaneous abortion, stillbirth, premature delivery and congenital defects have been observed following infection with wild-type measles during pregnancy {12,13}. Wild-type mumps infection during the first trimester of pregnancy may increase the rate of spontaneous abortion.

Infection with wild-type rubella during pregnancy can lead to miscarriage or stillbirth. If rubella infection occurs during the first trimester of pregnancy, it can result in severe congenital defects, Congenital Rubella Syndrome (CRS). Postmarketing surveillance has identified one case of CRS following inadvertent vaccination of a pregnant woman with a measles, mumps, and rubella virus containing vaccine from an unknown manufacturer{15}.

All pregnancies have a risk of birth defect, loss or other adverse outcomes. In the US general population, the estimated background risk of major birth defects and miscarriage in clinically recognized pregnancies is 2% to 4% and 15% to 20%, respectively.

Available data suggest the rates of major birth defects and miscarriage in women who received M-M-R II vaccine within 30 days prior to pregnancy or during pregnancy are consistent with estimated background rates (see Data).

Data

Human Data

A cumulative assessment of postmarketing reports for M-M-R II vaccine from licensure 01 April 1978 through 31 December 2018, identified 796 reports of inadvertent administration of M-M-R II vaccine occurring 30 days before or at any time during pregnancy with known pregnancy outcomes. Of the prospectively followed pregnancies for whom the timing of M-M-R II vaccination was known, 425 women received M-M-R II vaccine during the 30 days prior to conception through the second trimester. The outcomes for these 425 prospectively followed pregnancies included 16 infants with major birth defects, 4 cases of fetal death and 50 cases of miscarriage; no abnormalities compatible with CRS were identified.

The CDC established the Vaccine in Pregnancy registry (1971-1989) of women who had received rubella virus vaccines within 3 months before or after conception. Data on 1221 inadvertently vaccinated pregnant women demonstrated no evidence of an increase in fetal abnormalities or cases of CRS in the enrolled women {14}.

Postmarketing surveillance has identified a case of CRS associated with a rubella virus strain belonging to the genotype that includes the rubella virus strain Wistar RA 27/3 contained in M-M-R II. The infant with CRS was born to a pregnant woman who was inadvertently vaccinated at 5 weeks gestation with a measles, mumps, and rubella virus containing vaccine from an unknown manufacturer {15}.

Mumps vaccine virus has been shown to infect the placenta {16}, but there is no evidence that it causes congenital malformations or disease in the fetus or infant.

8.2 Lactation

Risk Summary

It is not known whether measles or mumps vaccine virus is secreted in human milk. Studies have shown that lactating postpartum women vaccinated with live attenuated rubella vaccine may secrete the virus in breast milk and transmit it to breast-fed infants. {17,18} In the breast-fed infants with serological evidence of rubella virus vaccine strain antibodies, none exhibited severe disease; however, one exhibited mild clinical illness typical of acquired rubella. {19,20}

The developmental and health benefits of breastfeeding should be considered along with the mother’s clinical need for M-M-R II, and any potential adverse effects on the breastfed child from M-M-R II or from the underlying maternal condition. For preventive vaccines, the underlying maternal condition is susceptibility to disease prevented by the vaccine.

8.4 Pediatric Use

M-M-R II vaccine is not approved for individuals less than 12 months of age. Safety and effectiveness of measles vaccine in infants below the age of 6 months have not been established [see Clinical Studies (14)]. Safety and effectiveness of mumps and rubella vaccine in infants less than 12 months of age have not been established.

8.5 Geriatric Use

Clinical studies of M-M-R II did not include sufficient numbers of seronegative subjects aged 65 and over to determine whether they respond differently from younger subjects.

11 DESCRIPTION

M-M-R II vaccine is a sterile lyophilized preparation of (1) Measles Virus Vaccine Live, an attenuated line of measles virus, derived from Enders' attenuated Edmonston strain and propagated in chick embryo cell culture; (2) Mumps Virus Vaccine Live, the Jeryl Lynn™ (B level) strain of mumps virus propagated in chick embryo cell culture; and (3) Rubella Virus Vaccine Live, the Wistar RA 27/3 strain of live attenuated rubella virus propagated in WI-38 human diploid lung fibroblasts. {21,22} The cells, virus pools, recombinant human serum albumin and fetal bovine serum used in manufacturing are tested and determined to be free of adventitious agents.

M-M-R II is an injectable suspension for intramuscular or subcutaneous use. After reconstitution, each approximately 0.5 mL dose contains not less than 3.0 log10 TCID50 (tissue culture infectious doses) of measles virus; 4.1 log10 TCID50 of mumps virus; and 3.0 log10 TCID50 of rubella virus.

Each dose is calculated to contain sorbitol (14.5 mg), sucrose (1.9 mg), hydrolyzed gelatin (14.5 mg), recombinant human albumin (≤0.3 mg), fetal bovine serum (<1 ppm), approximately 25 mcg of neomycin and other buffer and media ingredients. The product contains no preservative.

12 CLINICAL PHARMACOLOGY

12.1 Mechanism of Action

M-M-R II vaccination induces antibodies to measles, mumps, and rubella associated with protection which can be measured by neutralization assays, hemagglutination-inhibition (HI) assays, or enzyme linked immunosorbent assay (ELISA) tests. Results from efficacy studies or effectiveness studies that were previously conducted for the component vaccines of M-M-R II were used to define levels of serum antibodies that correlated with protection against measles, mumps, and rubella [see Clinical Studies (14)].

12.6 Persistence of Antibody Responses After Vaccination

Neutralizing and ELISA antibodies to measles, mumps, and rubella viruses are still detectable in 95-100%, 74-91%, and 90-100% of individuals respectively, 11 to 13 years after primary vaccination. {23-29}

13 NONCLINICAL TOXICOLOGY

13.1 Carcinogenesis, Mutagenesis, Impairment of Fertility

M-M-R II vaccine has not been evaluated for carcinogenic or mutagenic potential or impairment of fertility.

14 CLINICAL STUDIES

14.1 Clinical Efficacy

Efficacy of measles, mumps, and rubella vaccines was established in a series of double-blind controlled trials. {30-35} These studies also established that seroconversion in response to vaccination against measles, mumps and rubella paralleled protection. {36-39}

14.2 Immunogenicity

Clinical studies enrolling 284 triple seronegative children, 11 months to 7 years of age, demonstrated that subcutaneously administered M-M-R II vaccine is immunogenic. In these studies, a single subcutaneous injection of the vaccine induced measles HI antibodies in 95%, mumps neutralizing antibodies in 96%, and rubella HI antibodies in 99% of susceptible individuals.

A study of 6-month-old and 15-month-old infants born to mothers vaccinated with a measles vaccine in childhood, demonstrated that, following infant and toddler vaccination subcutaneously with Measles Virus Vaccine, Live (previously US-licensed, manufactured by Merck Sharp & Dohme LLC, Rahway, NJ, USA), 74% of the 6-month-old infants developed detectable neutralizing antibody titers while 100% of the 15-month-old infants vaccinated with Measles Virus Vaccine, Live or M-M-R II vaccine developed neutralizing antibodies {40}. When the 6-month-old infants of immunized mothers were revaccinated at 15 months with M-M-R II vaccine, they developed antibody titers similar to those of toddlers who were vaccinated previously at 15-months of age.

In an open label clinical trial (NCT00432523) 752 children 12 through 18 months of age received M-M-R II either intramuscularly (n=374) or subcutaneously (n=378), concomitantly with VARIVAX. Antibody responses to measles, mumps, and rubella viruses were measured by ELISAs using sera obtained 6 weeks postvaccination. For anti-measles virus, anti-mumps virus and anti-rubella virus, seroresponse rates were defined as the percentage of children seronegative at baseline who achieved antibody titers above the respective seroresponse threshold for each assay 6 weeks post vaccination. Seroresponse thresholds were defined as 255 mIU/mL, 10 EU/mL, and 10 IU/mL for anti-measles virus, anti-mumps virus, and anti-rubella virus antibodies, respectively. For each vaccine antigen at least 89% of enrolled children were seronegative at baseline. In a post hoc analysis, seroresponse rates to mumps and rubella viruses were noninferior for the intramuscular group compared to the subcutaneous group (the lower bound of the 95% confidence interval for the difference in seroresponse rates [intramuscular group minus subcutaneous group] ≥-5%). While the seroresponse rate to measles virus narrowly missed meeting the post hoc criterion of -5% for noninferiority (lower bound of the 95% CI for the difference in seroresponse rate -5.28%), it met the pre-specified criterion using a -10% noninferiority margin. For measles, mumps and rubella antigens the lower bound of the 95% CI of the seroresponse rates was ˃90% after intramuscular administration. The point estimates of the proportions of children achieving antibody titers above the seroresponse thresholds for measles, mumps, and rubella viruses were as follows: 94.3%, 97.7%, and 98.1%, respectively, in the intramuscular group and 96.1%, 98.1%, and 98.1%, respectively, in the subcutaneous group.

15 REFERENCES

1. General Recommendations on Immunization, Recommendations of the Advisory Committee on Immunization Practices, MMWR 43(RR-1): 1-38, January 28, 1994.
2. Measles, Mumps, and Rubella — Vaccine Use and Strategies for Elimination of Measles, Rubella, and Congenital Rubella Syndrome and Control of Mumps: Recommendations of the Advisory Committee on Immunization Practices (ACIP), MMWR 47(RR-8): May 22, 1998.
3. Kelso, J.M.; Jones, R.T.; Yunginger, J.W.: Anaphylaxis to measles, mumps, and rubella vaccine mediated by IgE to gelatin, J. Allergy Clin. Immunol. 91: 867-872, 1993.
4. Bitnum, A.; et al: Measles Inclusion Body Encephalitis Caused by the Vaccine Strain of Measles Virus. Clin. Infect. Dis. 29: 855-861, 1999.
5. Angel, J.B.; et al: Vaccine Associated Measles Pneumonitis in an Adult with AIDS. Annals of Internal Medicine, 129: 104-106, 1998.
6. Cecinati V, et al. Vaccine administration and the development of immune thrombocytopenic purpura in children. Human Vaccines & Immunotherapeutics 9:5, 2013.
7. Mantadakis E, Farmaki E, Buchanan GR. Thrombocytopenic Purpura after Measles-Mumps-Rubella Vaccination: A Systematic Review of the Literature and Guidance for Management. J Ped 156(4): 2010.
8. Andrews N, Stowe J, Miller E, Svanstrom H, Johansen K, Bonhoeffer J, et al. A collaborative approach to investigating the risk of thrombocytopenic purpura after measles-mumps-rubella vaccination in England and Denmark. Vaccine. 2012;30:3042-6.
9. Rubella Prevention: Recommendation of the Immunization Practices Advisory Committee (ACIP), MMWR 39(RR-15): 1-18, November 23, 1990.
10. Peter, G.; et al (eds): Report of the Committee on Infectious Diseases, Twenty-fourth Edition, American Academy of Pediatrics, 344-357, 1997.
11. Measles Prevention: Recommendations of the Immunization Practices Advisory Committee (ACIP), MMWR 38(S-9): 5-22, December 29, 1989.
12. Eberhart-Phillips, J.E.; et al: Measles in pregnancy: a descriptive study of 58 cases. Obstetrics and Gynecology, 82(5): 797-801, November 1993.
13. Jespersen, C.S.; et al: Measles as a cause of fetal defects: A retrospective study of ten measles epidemics in Greenland. Acta Paediatr Scand. 66: 367-372, May 1977.
14. Rubella Vaccination during Pregnancy —United States, 1971-1988. JAMA. 1989;261(23):3374–3383.
15. Bouthry, E.; Queinnec, C.; Vauzelle, C.; Vauloup-Fellous, C.: Congenital rubella syndrome following rubella vaccination during pregnancy. Pediatrics, 2023 Sep; 152 (3): e2022057627.
16. Yamauchi T, Wilson C, Geme JW Jr. Transmission of live, attenuated mumps virus to the human placenta. N Engl J Med. 1974;290(13):710-712.
17. Losonsky, G.A.; Fishaut, J.M.; Strussenber, J.; Ogra, P.L.: Effect of immunization against rubella on lactation products. II. Maternal-neonatal interactions, J. Infect. Dis. 145: 661-666, 1982.
18. Losonsky, G.A.; Fishaut, J.M.; Strussenber, J.; Ogra, P.L.: Effect of immunization against rubella on lactation products. I. Development and characterization of specific immunologic reactivity in breast milk, J. Infect. Dis. 145: 654-660, 1982.
19. Landes, R.D.; Bass, J.W.; Millunchick, E.W.; Oetgen, W.J.: Neonatal rubella following postpartum maternal immunization, J. Pediatr. 97: 465-467, 1980.
20. Lerman, S.J.: Neonatal rubella following postpartum maternal immunization, J. Pediatr. 98: 668, 1981. (Letter)
21. Plotkin, S.A.; Cornfeld, D.; Ingalls, T.H.: Studies of immunization with living rubella virus: Trials in children with a strain cultured from an aborted fetus, Am. J. Dis. Child. 110: 381-389, 1965.
22. Plotkin, S.A.; Farquhar, J.; Katz, M.; Ingalls, T.H.: A new attenuated rubella virus grown in human fibroblasts: Evidence for reduced nasopharyngeal excretion, Am. J. Epidemiol. 86: 468-477, 1967.
23. Weibel, R.E.; Carlson, A.J.; Villarejos, V.M.; Buynak, E.B.; McLean, A.A.; Hilleman, M.R.: Clinical and Laboratory Studies of Combined Live Measles, Mumps, and Rubella Vaccines Using the RA 27/3 Rubella Virus, Proc. Soc. Exp. Biol. Med. 165: 323-326, 1980.
24. Watson, J.C.; Pearson, J.S.; Erdman, D.D.; et al: An Evaluation of Measles Revaccination Among School-Entry Age Children, 31st Interscience Conference on Antimicrobial Agents and Chemotherapy, Abstract #268, 143, 1991.
25. Unpublished data from the files of Research Laboratories of Merck Sharp & Dohme LLC, Rahway, NJ, USA.
26. Davidkin, I.; Jokinen, S.; Broman, M. et al.: Persistence of Measles, Mumps, and Rubella Antibodies in an MMR-Vaccinated Cohort: A 20-Year Follow-up, JID 197:950–6, April 2008.
27. LeBaron, W.; Beeler J.; Sullivan, B.; et al.: Persistence of Measles Antibodies After 2 Doses of Measles Vaccine in a Postelimination Environment, Arch Pediatr Adolesc Med. 161:294-301, March 2007.
28. LeBaron, C.; Forghani, B.; Beck, C. et al.: Persistence of Mumps Antibodies after 2 Doses of Measles-Mumps-Rubella Vaccine, JID 199:552– 60 , February 2009.
29. LeBaron, W.; Forghani, B.; Matter, L. et al.: Persistence of Rubella Antibodies after 2 Doses of Measles-Mumps-Rubella Vaccine, JID 200:888–99, September 2009.
30. Hilleman, M.R.; Buynak, E.B.; Weibel, R.E.; et al: Development and Evaluation of the Moraten Measles Virus Vaccine, JAMA 206(3): 587-590, 1968.
31. Weibel, R.E.; Stokes, J.; Buynak, E.B.; et al: Live, Attenuated Mumps Virus Vaccine 3. Clinical and Serologic Aspects in a Field Evaluation, N. Engl. J. Med. 276: 245-251, 1967.
32. Hilleman, M.R.; Weibel, R.E.; Buynak, E.B.; et al: Live, Attenuated Mumps Virus Vaccine 4. Protective Efficacy as Measured in a Field Evaluation, N. Engl. J. Med. 276: 252-258, 1967.
33. Cutts, F.T.; Henderson, R.H.; Clements, C.J.; et al: Principles of measles control, Bull WHO 69(1): 1-7, 1991.
34. Weibel, R.E.; Buynak, E.B.; Stokes, J.; et al: Evaluation Of Live Attenuated Mumps Virus Vaccine, Strain Jeryl Lynn, First International Conference on Vaccines Against Viral and Rickettsial Diseases of Man, World Health Organization, No. 147, May 1967.
35. Leibhaber, H.; Ingalls, T.H.; LeBouvier, G.L.; et al: Vaccination With RA 27/3 Rubella Vaccine, Am. J. Dis. Child. 123: 133-136, February 1972.
36. Rosen, L.: Hemagglutination and Hemagglutination-Inhibition with Measles Virus, Virology 13: 139-141, January 1961.
37. Brown, G.C.; et al: Fluorescent-Antibody Marker for Vaccine-Induced Rubella Antibodies, Infection and Immunity 2(4): 360-363, 1970.
38. Buynak, E.B.; et al: Live Attenuated Mumps Virus Vaccine 1. Vaccine Development, Proceedings of the Society for Experimental Biology and Medicine, 123: 768-775, 1966.
39. Hilleman M.R., Studies of Live Attenuated Measles Virus Vaccine in Man: II. Appraisal of Efficacy. Amer. J. of Public Health, 52(2):44-56, 1962.
40. Johnson, C.E.; et al: Measles Vaccine Immunogenicity in 6- Versus 15-Month-Old Infants Born to Mothers in the Measles Vaccine Era, Pediatrics, 93(6): 939-943, 1994.

16 HOW SUPPLIED/STORAGE AND HANDLING

M-M-R II vaccine is supplied as follows:
(1) a box of 10 single-dose vials of lyophilized vaccine (package A), NDC 0006-4681-00
(2) a box of 10 prefilled syringes of sterile diluent, NDC 0006-4175-88 (package B) OR a box of 10 vials of sterile diluent, NDC 0006-4309-00 (package B)

Storage

Vaccine Vial

Exposure to light may inactivate the vaccine viruses.

To maintain potency, M-M-R II must be stored between -58°F and +46°F (-50°C to +8°C). Use of dry ice may subject M-M-R II to temperatures colder than -58°F (-50°C).

Before reconstitution, refrigerate the lyophilized vaccine at 36°F to 46°F (2°C to 8°C).

Sterile Diluent

The sterile diluent should be stored in the refrigerator (36°F to 46°F, 2°C to 8°C) or at room temperature (68°F to 77°F, 20°C to 25°C). Do not freeze the sterile diluent.

Administer M-M-R II vaccine immediately after reconstitution. If not administered immediately, reconstituted vaccine may be stored between 36°F to 46°F (2°C to 8°C), protected from light, for up to 8 hours. Discard reconstituted vaccine if it is not used within 8 hours.

For information regarding the product or questions regarding storage conditions, call 1-800-637-2590.

17 PATIENT COUNSELING INFORMATION

Advise the patient to read the FDA-approved patient labeling (Patient Package Insert).

Discuss the following with the patient:

- Provide the required vaccine information to the patient, parent, or guardian.
- Inform the patient, parent, or guardian of the benefits and risks associated with vaccination.
- Question the patient, parent, or guardian about reactions to a previous dose of M-M-R II vaccine or other measles-, mumps-, or rubella-containing vaccines.
- Question females of reproductive potential regarding the possibility of pregnancy prior to administration of M-M-R II. Instruct these individuals to avoid pregnancy for 1 month following vaccination [see Contraindications (4.5) and Use in Specific Populations (8.1)].
- Inform the patient, parent, or guardian that vaccination with M-M-R II may not offer 100% protection from measles, mumps, and rubella infection.
- Instruct patients, parents, or guardians to report any adverse reactions to their health-care provider. The U.S. Department of Health and Human Services has established a Vaccine Adverse Event Reporting System (VAERS) to accept all reports of suspected adverse events after the administration of any vaccine, including but not limited to the reporting of events required by the National Childhood Vaccine Injury Act of 1986. For information or a copy of the vaccine reporting form, call the VAERS toll-free number at 1-800-822-7967, or report online at https://www.vaers.hhs.gov .

Distributed by: Merck Sharp & Dohme LLC
Rahway, NJ 07065, USA

For patent information: www.msd.com/research/patent

Copyright © 1978-2025 Merck & Co., Inc., Rahway, NJ, USA, and its affiliates.
All rights reserved.

uspi-v205c-i-2511r016

Patient Information
M-M-R® II (pronounced “em em ar too”)
Measles, Mumps, and Rubella Virus Vaccine Live

This is a summary of information about M-M-R® II. You should read it before you or your child receives the vaccine. If you have any questions about the vaccine after reading this leaflet, you should ask your health care provider. This is a summary only. It does not take the place of talking about M-M-R II with your doctor, nurse, or other health care provider. Only your health care provider can decide if M-M-R II is right for you or your child.

What is M-M-R II and how does it work?

M-M-R II is also known as Measles, Mumps, and Rubella Virus Vaccine Live. It is a live virus vaccine that is given as a shot. This vaccine is usually given to people one year old or older. It is meant to help prevent measles (rubeola), mumps, and rubella (German measles).

M-M-R II contains weakened forms of measles virus, mumps virus, and rubella virus.

M-M-R II works by helping the immune system protect you or your child from getting measles, mumps, or rubella.

M-M-R II may not protect everyone who gets the vaccine. M-M-R II does not treat measles, mumps, or rubella once you or your child has them.

What do I need to know about measles, mumps, and rubella?

Measles is also known as rubeola. It is a serious illness. Measles virus can be passed to others if you have it. Measles can give you a high fever, cough, and a rash. The illness can last for 1 to 2 weeks. In rare cases, it can also cause an infection of the brain. This could lead to seizures, hearing loss, intellectual disability, and even death.

Mumps can also be passed to others. This virus can cause fever and headache. It can also make the glands under your jaw swell and be painful. The illness often lasts for several days. Sometimes, mumps can make the testicles swell and be painful. In some cases, it can cause meningitis, which is a swelling of the coverings of the brain and spinal cord.

Rubella is also known as German measles. It is often a mild illness. Rubella virus can cause a mild fever, swollen glands in the neck, pain and swelling in the joints, and a rash that lasts for a short time. It can be very dangerous if a pregnant woman catches it. Women who catch German measles when they are pregnant can have babies who are stillborn. Also, the babies may be blind or deaf, or have heart disease or intellectual disability.

Who should not get M-M-R II?

Do not get M-M-R II if you or your child:

- are allergic to any of its ingredients. (This includes gelatin. See the ingredient list at the end of this leaflet.)
- have a weakened immune system (which includes taking high doses of steroids by mouth or in a shot).
- have a fever.
- have active tuberculosis that is not treated.
- are pregnant or plan to get pregnant within the next month.

What should you tell your health care provider before getting M-M-R II?

Tell your health care provider if you or your child:

- have or have had any medical problems.
- have a history of seizures or someone in your family has a history of seizures.
- have received blood or plasma transfusions or human serum globulin.
- take any medicines. (This includes non-prescription medicines and dietary supplements.)
- have any allergies.
- had an allergic reaction to any other vaccine.
- have or have had a low blood platelet count.
- are allergic to eggs.

How is M-M-R II given?

M-M-R II is given as a shot to people one year old or older. The dose of the vaccine is the same for everyone. If your child gets the shot when he or she is one year old or older, a second dose is recommended. Often, the second dose is given right before the child goes to elementary school (4 to 6 years of age), but may be given earlier as long as the second dose is at least one month after the first dose.

If your child is less than one year old when he or she first gets the shot, a second dose should be given when they are 12 to 15 months old. Then, a third shot should be given between 4 and 6 years of age. Your doctor will decide the best time and number of shots by using official recommendations.

If a dose is missed, your health care provider will let you know when you should have it.

What are the possible side effects of M-M-R II?

The most common side effect of vaccination with M-M-R II is pain at the site of the shot for a short time.

Other side effects may include:

- Fever
- Rash

Less common side effects may also include:

- Swelling of the testicles
- Joint pain and/or swelling

Some side effects are rare but may be serious. You should call your health care provider if you notice any of the following problems:

- Difficulty breathing, wheezing, hives, or a skin rash may be signs of an allergic reaction
- Bleeding or bruising under the skin
- Seizures, a severe headache, a change in behavior or consciousness, or difficulty walking

Other side effects may also occur. Your doctor has a more complete list of side effects for M-M-R II.

Contact your doctor or health care provider if you or your child have any new or unusual symptoms after receiving M-M-R II.

Report the following to your doctor or your child’s doctor:

- exposure to M-M-R II during pregnancy
- exposure to M-M-R II during the month before getting pregnant

You may also report any adverse reactions to your doctor or your child's health care provider or submit a report directly to the Vaccine Adverse Event Reporting System (VAERS). The VAERS toll-free number is 1-800-822-7967 or you may report online to www.vaers.hhs.gov .

What are the ingredients of M-M-R II?

Active Ingredients: weakened forms of the measles, mumps, and rubella viruses.

Inactive Ingredients: sorbitol, sucrose, hydrolyzed gelatin, recombinant human albumin, fetal bovine serum, other buffer and media ingredients, neomycin.

What else should I know about M-M-R II?

This leaflet summarizes important information about M-M-R II.

If you would like more information, talk to your health care provider or call 1-800-622-4477.

Dist. by: Merck Sharp & Dohme LLC
Rahway, NJ 07065, USA

For patent information: www.msd.com/research/patent

Copyright © 1978-2023 Merck & Co., Inc., Rahway, NJ, USA, and its affiliates.
All rights reserved.

usppi-v205c-i-2303r206

This Patient Information has been approved by the U.S. Food and Drug Administration. Revised: 03/2023

PRINCIPAL DISPLAY PANEL - 0.5 mL Vial Carton

NDC 0006-4681-00

10 Single-dose 0.5-mL vials

MEASLES, MUMPS, AND RUBELLA VIRUS VACCINE LIVE
M-M-R® II

Measles: attenuated Enders' strain/chick embryo cell culture.
Mumps: Jeryl Lynn™ strain/chick embryo cell culture.
Rubella: Wistar RA 27/3 strain/WI-38 human diploid lung fibroblasts.
No preservative
Rx only

A

MERCK

PRINCIPAL DISPLAY PANEL - 0.7 mL Syringe

NDC 0006-4175-88

10 Single-Dose 0.7-mL Syringes

STERILE DILUENT

FOR MERCK SHARP & DOHME LLC
LIVE VIRUS VACCINES
(Sterile Water)

CONTAINS NO PRESERVATIVE

This carton contains 10 prefilled syringes. Each prefilled syringe
contains 0.7 mL of sterile diluent. Use one prefilled syringe for
reconstitution of one single-dose vial of live virus vaccine.

Rx only

B

PRINCIPAL DISPLAY PANEL - 0.7 mL Syringe

NDC 0006-4175-89

CONTAINS NO PRESERVATIVE

1 Single-Dose 0.7-mL
Syringe

STERILE DILUENT

FOR MERCK SHARP & DOHME LLC
LIVE VIRUS VACCINES
(Sterile Water)

Rx only

Manufactured for:
Merck Sharp & Dohme LLC
By: Baxter Pharmaceutical Solutions, LLC

PRINCIPAL DISPLAY PANEL - 0.7 mL Vial

NDC 0006-4309-00

10 Single-Dose
0.7-mL Vials

STERILE DILUENT

FOR MERCK SHARP & DOHME LLC
LIVE VIRUS VACCINES
(Sterile Water)

CONTAINS NO PRESERVATIVE

This carton contains 10 diluent-containing vials. Use one diluent vial
for reconstitution of one single-dose vial of live virus vaccine.

Rx only

B

PRINCIPAL DISPLAY PANEL - 0.7 mL Vial

NDC 0006-4309-01

1 Single-Dose 0.7-mL Vial

STERILE DILUENT

FOR MERCK SHARP & DOHME LLC
LIVE VIRUS VACCINES
(Sterile Water)

Rx only

CONTAINS NO
PRESERVATIVE